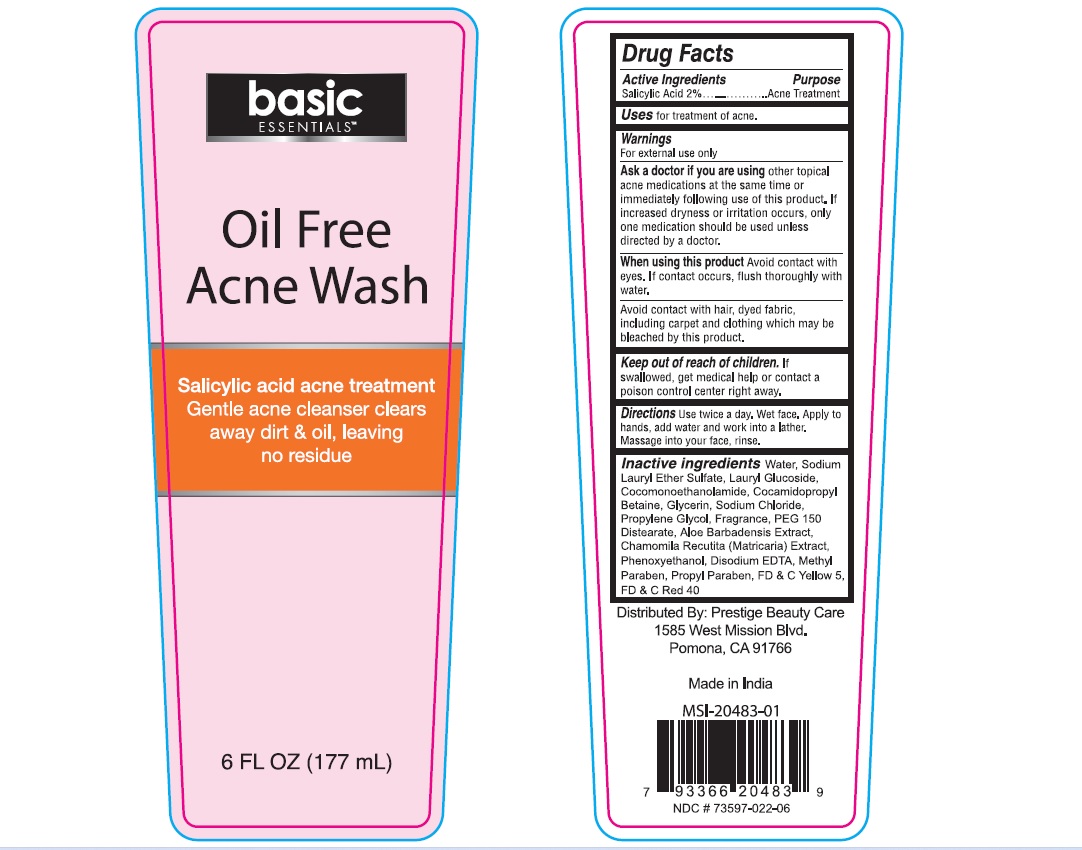 DRUG LABEL: Basic Essential Oil Free Acne Wash
NDC: 73597-022 | Form: LIQUID
Manufacturer: Mission Series Inc. dba Prestige Beauty Care
Category: otc | Type: HUMAN OTC DRUG LABEL
Date: 20230628

ACTIVE INGREDIENTS: SALICYLIC ACID 2 g/100 mL
INACTIVE INGREDIENTS: WATER; SODIUM LAURETH-3 SULFATE; LAURYL GLUCOSIDE; COCO MONOETHANOLAMIDE; COCAMIDOPROPYL BETAINE; GLYCERIN; SODIUM CHLORIDE; PROPYLENE GLYCOL; PEG-150 DISTEARATE; ALOE VERA LEAF; CHAMOMILE FLOWER OIL; PHENOXYETHANOL; EDETATE DISODIUM ANHYDROUS; METHYLPARABEN; PROPYLPARABEN; FD&C YELLOW NO. 5; FD&C RED NO. 40

Active Ingredient

Salicyclic Acid 2%

Purpose

Acne Treatment

Uses

for treatment of acne.

Warnings

For external use only.

Ask a doctor if you are usingother topical acne medications at the same time or immediately following use of this product. If increased dryness or irritation occurs, only one medication should be used unless directed by a doctor.

When using this productAvoid contact with eyes. If contact occurs, flush thoroughly with water.

Avoid contact with hair, dyed fabric, including carpet and clothing which may be bleached by this product.

Keep out of reach of children

If swallowed, get medical help or contact a Poison Control Center right away.

Directions

Use twice a day, Wet face, Apply to hands, add water and work into a lather. Massage into your face, rinse.

Inactive Ingredients

Water, Sodium Lauryl Ether Sulfate, Lauryl Glucoside, Cocomonoethanolamide, Cocamidopropyl Betaine, Glycerin, Sodium Chloride, Propylene Glycol, Fragrance, PEG 150 Distearate, Aloe Barbadensis Extract, Chamomila Recutita (Matricaria) Extract, Phenoxyethanol, Disodium EDTA, Methyl paraben, Propyl Paraben, FD & C Yellow 5, FD & C Red 40

Distributed By:

PRESTIGE BEAUTY CARE

1585 West Mission Blvd.

Pomona, CA 91766

Made in India